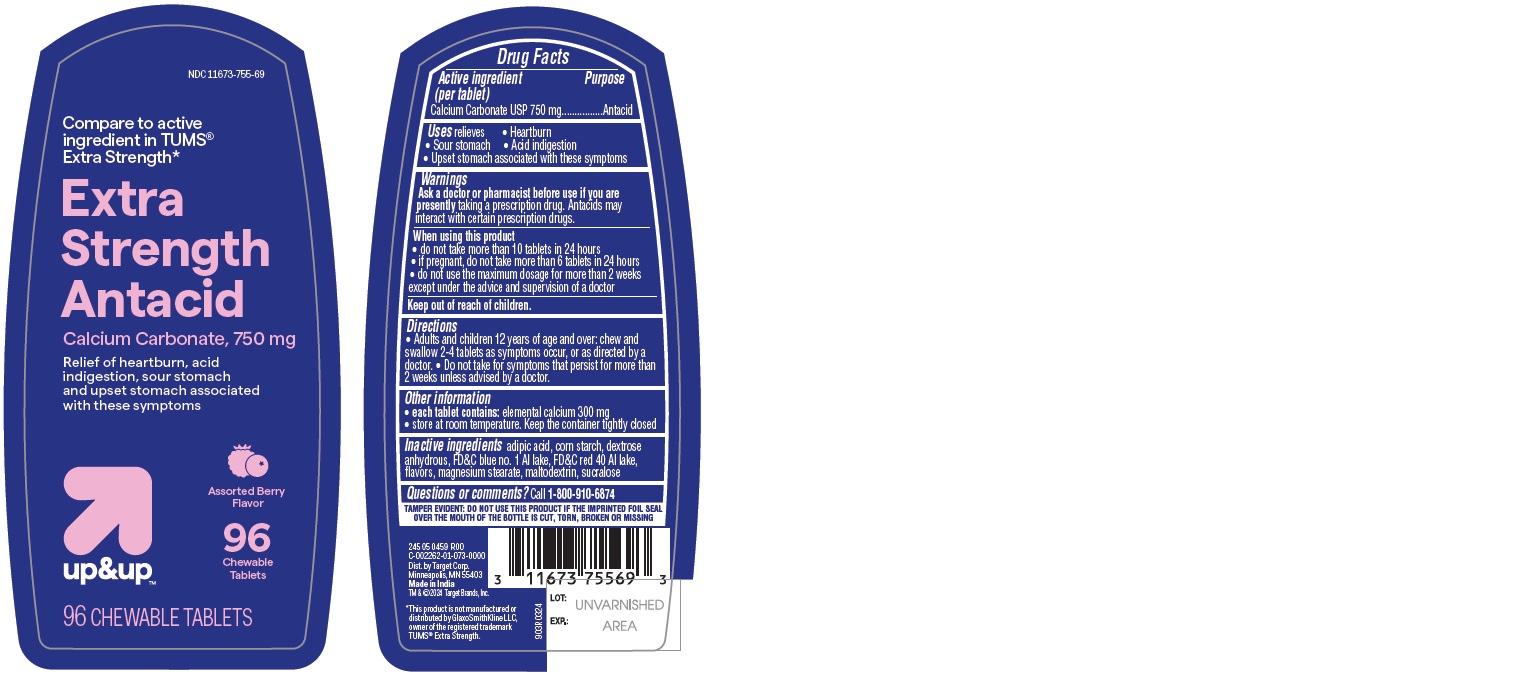 DRUG LABEL: Extra Strength Antacid Calcium Carbonate,750 mg
NDC: 11673-755 | Form: TABLET, CHEWABLE
Manufacturer: TARGET CORPORATION
Category: otc | Type: HUMAN OTC DRUG LABEL
Date: 20251104

ACTIVE INGREDIENTS: CALCIUM CARBONATE 750 mg/1 1
INACTIVE INGREDIENTS: FD&C BLUE NO. 1; MALTODEXTRIN; ADIPIC ACID; STARCH, CORN; MAGNESIUM STEARATE; SUCRALOSE; ANHYDROUS DEXTROSE; FD&C RED NO. 40

903R-Target-11673-755-Extra strength antacid Calcium Carbonate

Active ingredient (per tablet)

Calcium Carbonate USP 750 mg

Purpose

Antacid

Uses

relieves

- Heartburn
- Sour stomach
- Acid indigestion
- Upset stomach associated with these symptoms

Warnings

Ask a doctor or pharmacist before use if you are presently

taking a prescription drug. Antacids may interact with certain prescription drugs.

When using this product

- do not take more than 10 tablets in 24 hours
- if pregnant, do not take more than 6 tablets in 24 hours
- do not use the maximum dosage for more than 2 weeks except under the advice and supervision of a doctor

Directions

- Adults and children 12 years of age and over: chew and swallow 2-4 tablets as symptoms occur, or as directed by a doctor.
- Do not take for symptoms that persist for more than 2 weeks unless advised by a doctor.

Other information

- each tablet contains: elemental calcium 300 mg
- store at room temperature. Keep the container tightly closed.

Inactive ingredients

adipic acid, corn starch, dextrose anhydrous, FD&C blue no. 1 Al lake, FD&C red 40 Al lake, flavors, magnesium stearate, maltodextrin, sucralose

Questions or comments?

Call 1-800-910-6874